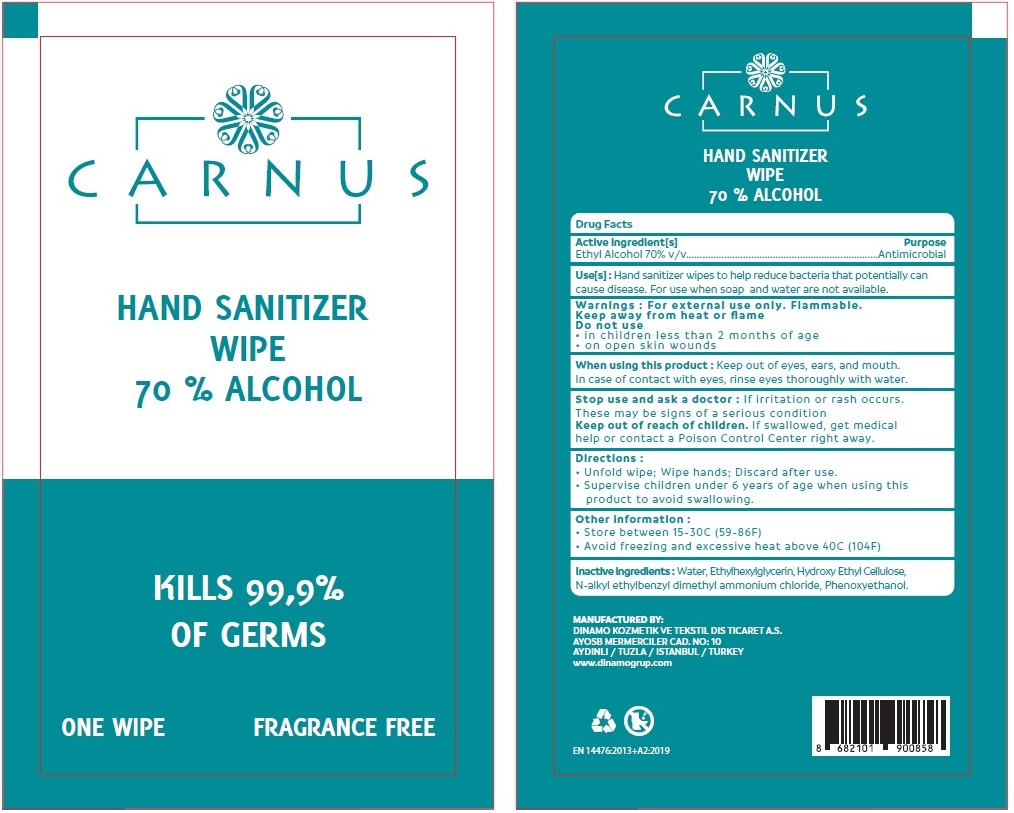 DRUG LABEL: CARNUS HAND SANITIZER WIPES
NDC: 79853-105 | Form: CLOTH
Manufacturer: DINAMO KOZMETIK VE TEKSTIL DIS TICARET ANONIM SIRKETI
Category: otc | Type: HUMAN OTC DRUG LABEL
Date: 20200819

ACTIVE INGREDIENTS: ALCOHOL 70 mL/100 mL
INACTIVE INGREDIENTS: WATER; ETHYLHEXYLGLYCERIN; HYDROXYETHYL CELLULOSE, UNSPECIFIED; N-ALKYL ETHYLBENZYL DIMETHYL AMMONIUM CHLORIDE (C12-C14); PHENOXYETHANOL

CARNUS HAND SANITIZER WIPE

Active ingredient[s]

Ethyl Alcohol 70% v/v

Purpose

Antimicrobial

Use[s] :

Hand sanitizer wipes to help reduce bacteria that potentially can cause disease. For use when soap and water are not available.

Warnings :

For external use only. Flammable.

Keep away from heat or flame

Do not use

• in children less than 2 months of age

• on open skin wounds

When using this product : Keep out of eyes, ears, and mouth. In case of contact with eyes, rinse eyes thoroughly with water.

Stop use and ask a doctor : If irritation or rash occurs. These may be signs of a serious condition

Keep out of reach of children. If swallowed, get medical help or contact a Poison Control Center right away.

Directions :

• Unfold wipe; Wipe hands; Discard after use.

• Supervise children under 6 years of age when using this product to avoid swallowing.

Other information :

• Store between 15-30C (59-86F)

• Avoid freezing and excessive heat above 40C (104F)

Inactive ingredients :

Water, Ethylhexylglycerin, Hydroxy Ethyl Cellulose, N-alkyl ethylbenzyl dimethyl ammonium chloride, Phenoxyethanol.

70 % ALCOHOL

KILLS 99,9% OF GERMS

FRAGRANCE FREE

MANUFACTURED BY:

DINAMO KOZMETIK VE TEKSTIL DIS TICARET A.S.

AYOSB MERMERCILER CAD. NO: 10

AYDINLI / TUZLA / ISTANBUL / TURKEY

www.dinamogrup.com

EN 14476:2013+A2:2019